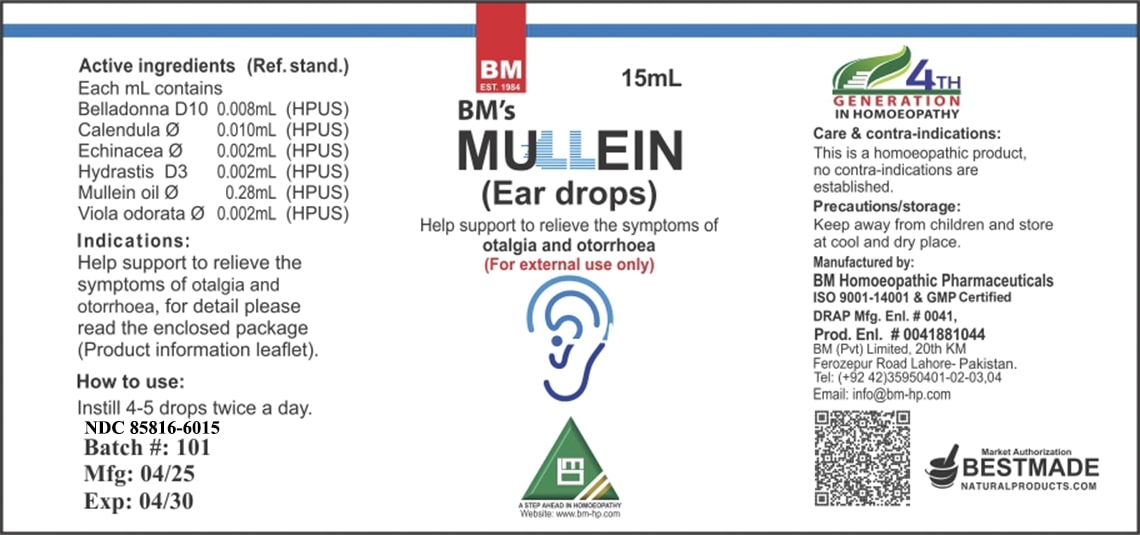 DRUG LABEL: BM Natural Mullein Ear
NDC: 85816-6015 | Form: SOLUTION/ DROPS
Manufacturer: BM Private Limited
Category: homeopathic | Type: HUMAN OTC DRUG LABEL
Date: 20250627

ACTIVE INGREDIENTS: VIOLA ODORATA 1 [hp_X]/1 mL; ATROPA BELLADONNA 10 [hp_X]/1 mL; CALENDULA OFFICINALIS FLOWERING TOP 1 [hp_X]/1 mL; VERBASCUM THAPSUS 1 [hp_X]/1 mL; ECHINACEA, UNSPECIFIED 1 [hp_X]/1 mL; GOLDENSEAL 3 [hp_X]/1 mL
INACTIVE INGREDIENTS: PROPYLPARABEN 0.6 mg/1 mL; METHYLPARABEN 1 mg/1 mL; GLYCERIN 0.27 mL/1 mL; WATER 0.38 mL/1 mL; ALCOHOL 0.35 mL/1 mL

BM Natural Mullein Ear Drops

INACTIVE INGREDIENT

Ethanol 35%, Distilled water, Glycerin, Methyl paraben, Propyl paraben

ACTIVE INGREDIENT

Active ingredients (Ref. stand.) Each mL contains Belladonna D10 0.008mL (HPUS) Calendula ∅ 0.010mL (HPUS) Echinacea ∅ 0.002mL (HPUS) Hydrastis D3 0.002mL (HPUS) Mullein oil ∅ 0.28mL (HPUS) Viola odorata ∅ 0.002mL (HPUS)

INDICATIONS AND USAGE

Indications: Help support to relieve the symptoms of otalgia and otorrhoea, for detail please read the enclosed package (Product information leaflet).

PURPOSE

Indications: Help support to relieve the symptoms of otalgia and otorrhoea, for detail please read the enclosed package (Product information leaflet).

DOSAGE AND ADMINISTRATION

How to use: Instill 4-5 drops twice a day.

CONTRAINDICATIONS

Care & contra-indications: This is a homeopathic product, no contra-indications are established.

WARNINGS

Precautions/storage: Keep away from children and store at cool and dry place.

KEEP OUT OF REACH OF CHILDREN

Precautions/storage: Keep away from children and store at cool and dry place.

STORAGE AND HANDLING

Precautions/storage: Keep away from children and store at cool and dry place.

Entire package label